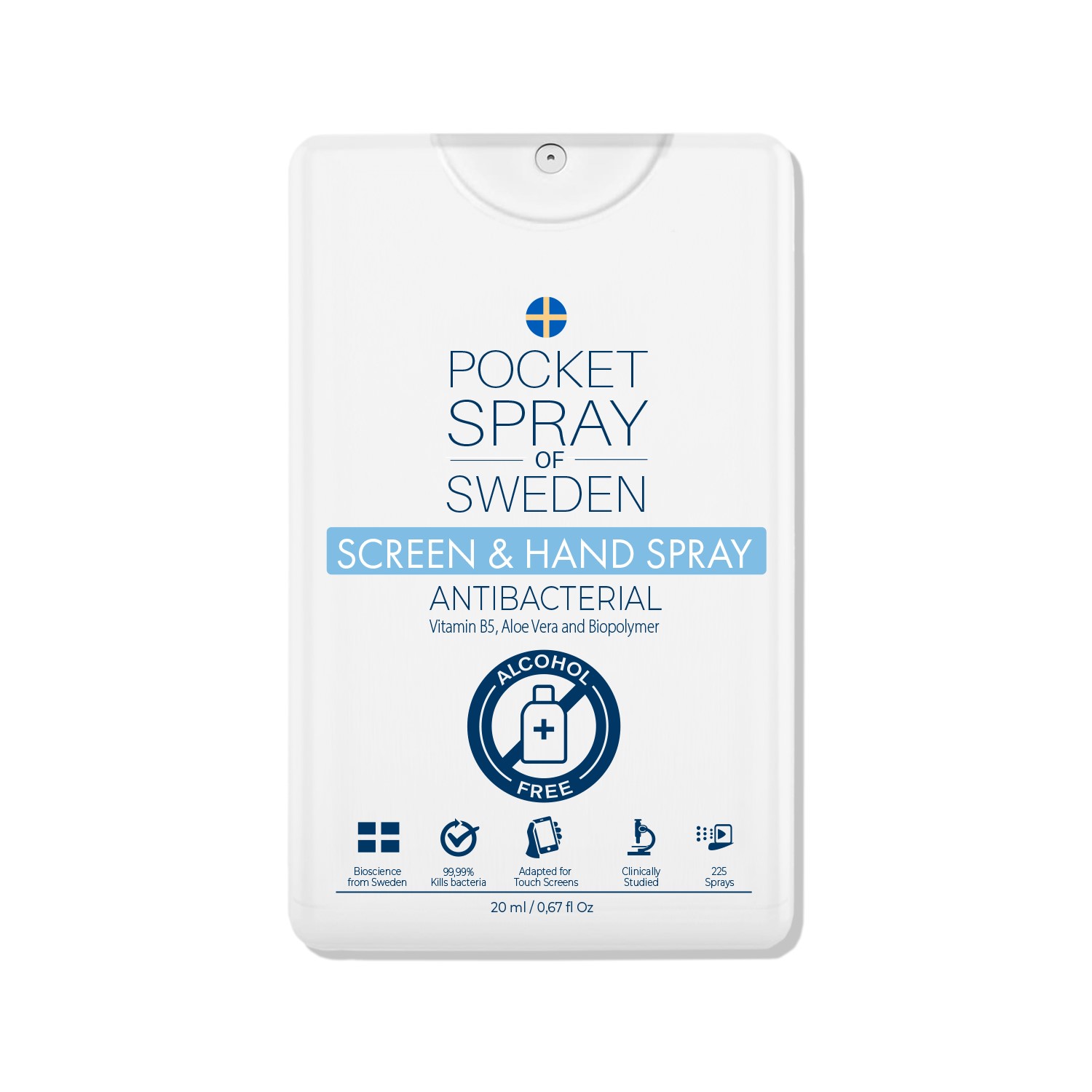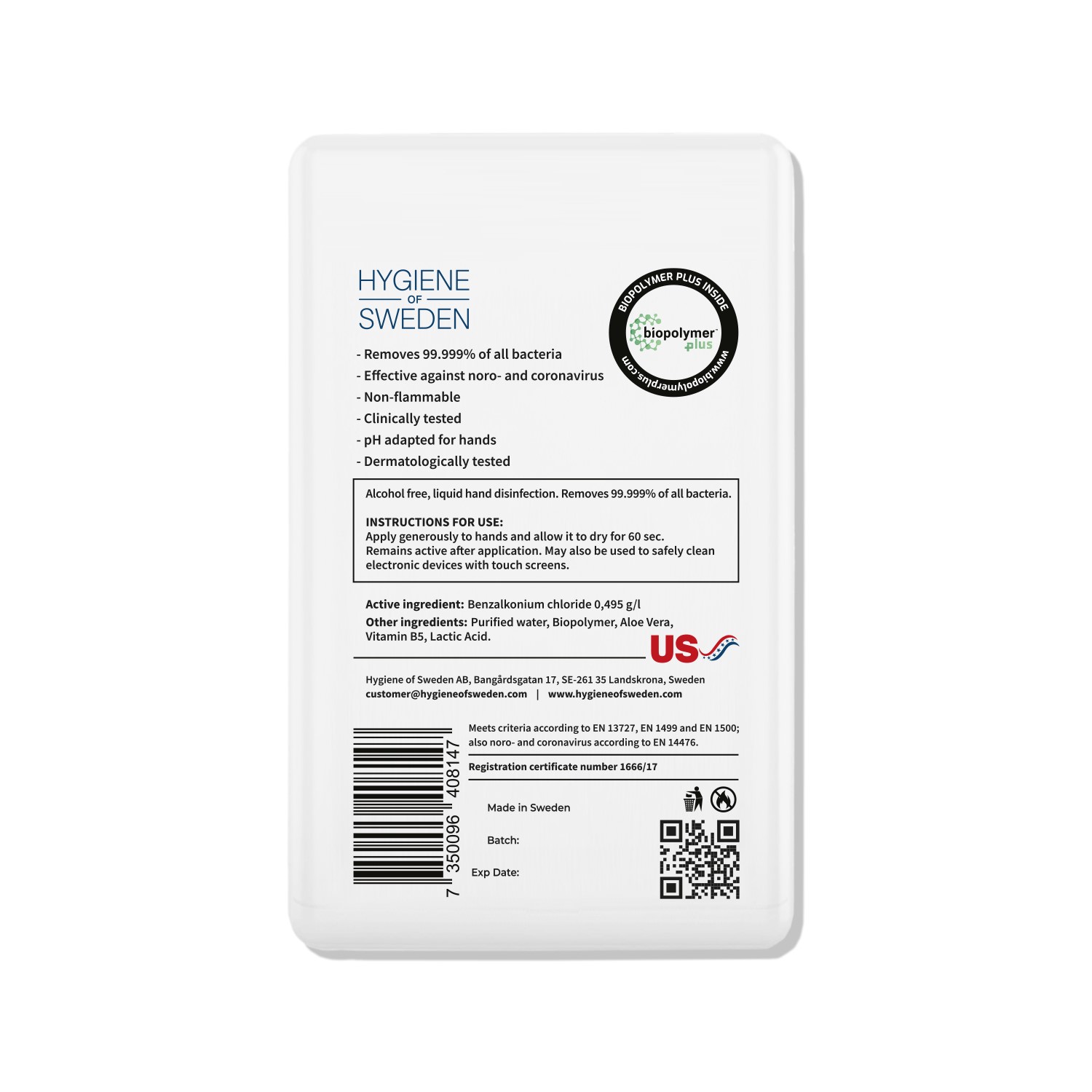 DRUG LABEL: Hygiene of Sweden
NDC: 81274-001 | Form: AEROSOL, SPRAY
Manufacturer: Hygiene of Sweden AB
Category: otc | Type: HUMAN OTC DRUG LABEL
Date: 20220318

ACTIVE INGREDIENTS: BENZALKONIUM CHLORIDE 9.9 mg/100 mL
INACTIVE INGREDIENTS: LACTIC ACID 0.03 mL/100 mL; CHITOSAN MEDIUM MOLECULAR WEIGHT (200-400 MPA.S) 0.02 mL/100 mL; POLYETHYLENIMINE HYDROCHLORIDE (20000 MW) 0.01 mL/100 mL; PHENOXYETHANOL 0.25 mL/100 mL; DEXPANTHENOL 0.01 mL/100 mL; WATER 99.48 mL/100 mL; ALOE VERA LEAF 0.1 mL/100 mL

Hand sanitizer

Active Ingredients

Benzalkonium Chloride 0,495 g/l

DOSAGE AND ADMINISTRATION

Apply generously to hands and allow it to dry for 60 seconds.

WARNINGS

Avoid contact with eyes. If contact occurs, rinse thoroughly with water.

INACTIVE INGREDIENT

Purified water, Biopolymer, Aloe Vera, Vitamin B5, Lactic Acid

INDICATIONS AND USAGE

Antibacterial. Spray on hands and rub, allow 60 seconds to dry.

PURPOSE

Antibacterial

KEEP OUT OF REACH OF CHILDREN

N/A

PACKAGE LABEL

81274-001-01